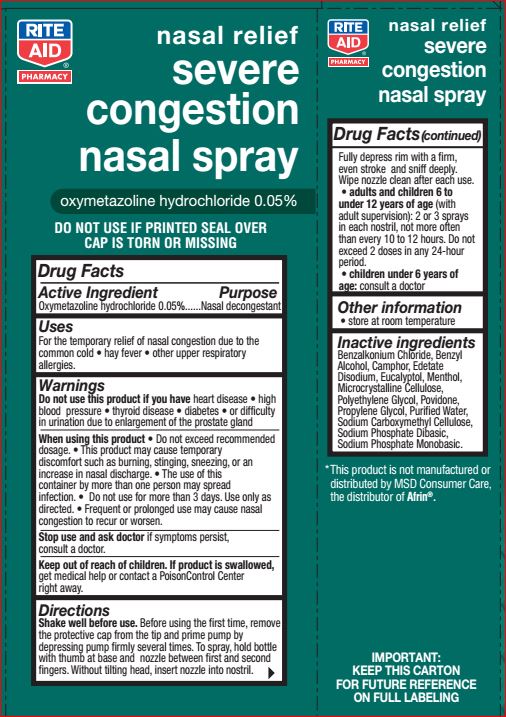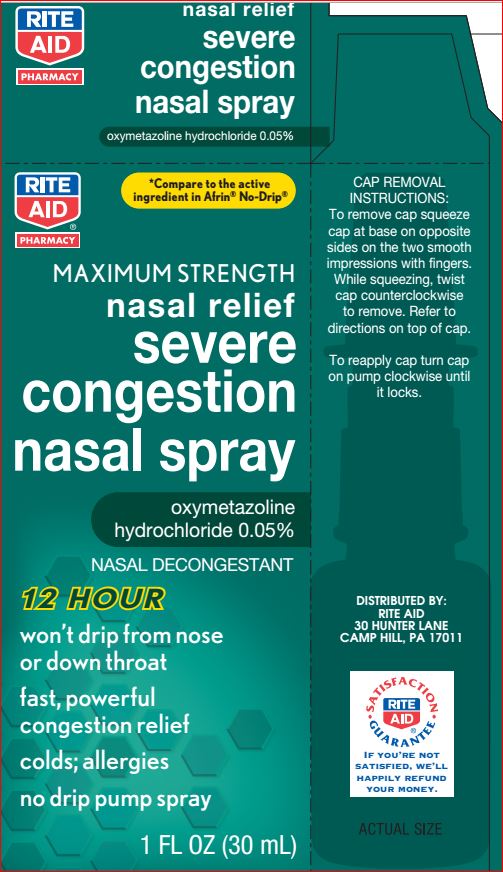 DRUG LABEL: Max Str.Nasal Relief Severe Congestion
NDC: 11822-1232 | Form: LIQUID
Manufacturer: Ride Aid
Category: otc | Type: HUMAN OTC DRUG LABEL
Date: 20180618

ACTIVE INGREDIENTS: Oxymetazoline Hydrochloride 0.05 g/100 mL
INACTIVE INGREDIENTS: Benzalkonium Chloride; Benzyl Alcohol; CAMPHOR (SYNTHETIC); Edetate Disodium; Eucalyptol; Menthol; CELLULOSE, MICROCRYSTALLINE; POLYETHYLENE GLYCOLS; Povidone; Propylene Glycol; Water; CARBOXYMETHYLCELLULOSE SODIUM, UNSPECIFIED FORM; SODIUM PHOSPHATE, DIBASIC, ANHYDROUS; SODIUM PHOSPHATE, MONOBASIC, ANHYDROUS

Drug Facts

Active ingredient Purpose

Oxymetazoline Hydrochloride 0.05% Nasal decongestant

Uses

• for the temporary relief of nasal congestion due to
the common cold, hay fever or other upper respiratory
allergies

Warnings

Ask a doctor before use if you have
• heart disease• high blood pressure• thyroid disease
• diabetes• trouble urinating due to enlarged prostate gland

When using this product

Do not use this product if you have heart disease • high
blood pressure • thyroid disease • diabetes • or difficulty
in urination due to enlargement of the prostate gland
When using this product • Do not exceed recommended
dosage. • This product may cause temporary
discomfort such as burning, stinging, sneezing, or an
increase in nasal discharge. • The use of this
container by more than one person may spread
infection. • Do not use for more than 3 days. Use only as
directed. • Frequent or prolonged use may cause nasal
congestion to recur or worsen.
Stop use and ask doctor if symptoms persist,
consult a doctor.

Keep out of reach of children. If product is swallowed, get medical help or contact a PoisonControl Center right away.

Directions

Before using the first time, remove the protective cap from the tip and prime pump by depressing pump firmly several times.
To spray, hold bottle with thumb at base and nozzle between first and second fingers. Without tilting head, insert nozzle into nostril. Fully depress rim with a firm, even stroke and sniff deeply. Wipe nozzle clean after use. • adults and children 6 to under12 years of age (with adult supervision): 2 or 3 sprays in each nostril not more often than every 10 to 1 2 hours. Do not exceed 2 doses within any 24-hour period • children under 6 years of age: consult a doctor

Inactive ingredients

Benzalkonium Chloride, Benzyl Alcohol, Camphor, Edetate Disodium, Eucalyptol, Menthol, Microcrystalline Cellulose, Polyethylene Glycol, Povidone, Propylene Glycol, Purified Water, Sodium Carboxymethyl Cellulose, Sodium Phosphate Dibasic, Sodium Phosphate Monobasic.